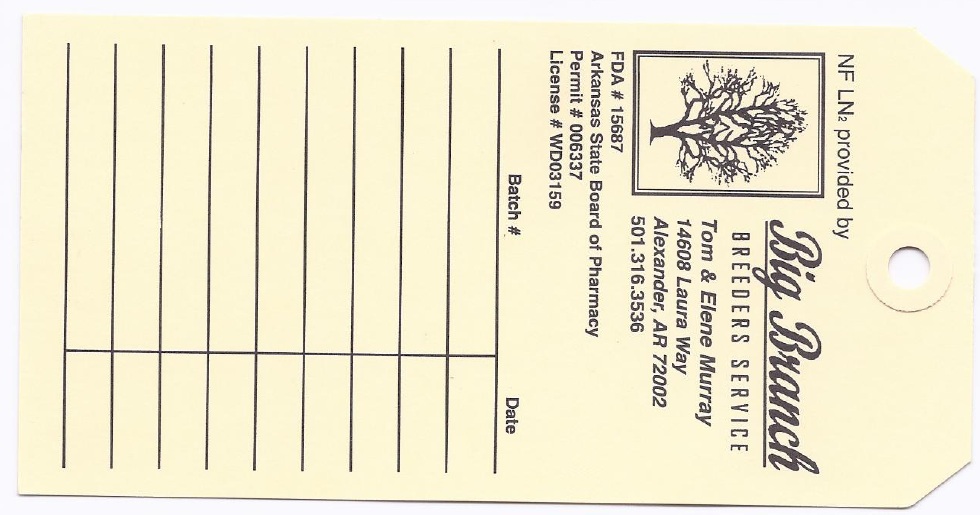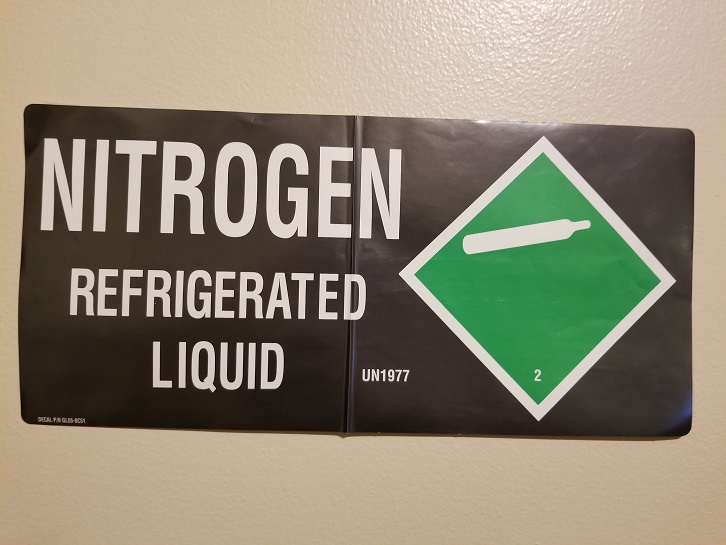 DRUG LABEL: Nitrogen
NDC: 15687-001 | Form: GAS
Manufacturer: Big Branch Breeders Service
Category: prescription | Type: HUMAN PRESCRIPTION DRUG LABEL
Date: 20251107

ACTIVE INGREDIENTS: NITROGEN 990 mL/1 L

Nitrogen

PACKAGE LABEL

NF LN2 provided by big Branch BREEDERS SERVICE

Tom and Elene Murray

14608 Laura Way

Alexander, AR 72002

501.316.3536

FDA # 15678

Arkansas State Board of Pharmacy

Permit # 006337

License # WD03159

Batch # Date

PACKAGE LABEL

Nitrogen Refrigerated Liquid UN1977 2